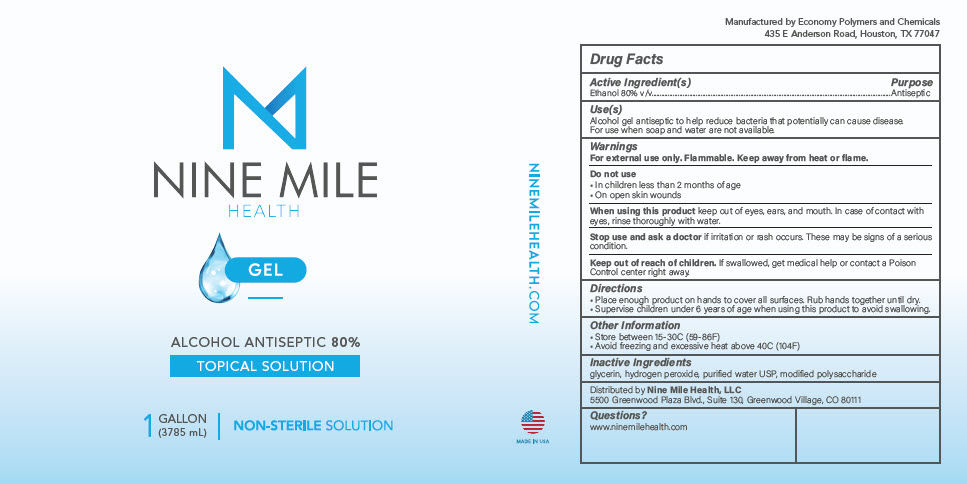 DRUG LABEL: Hand Sanitizer Gel
NDC: 78697-128 | Form: LIQUID
Manufacturer: Nine Mile Health, LLC
Category: otc | Type: HUMAN OTC DRUG LABEL
Date: 20200707

ACTIVE INGREDIENTS: Alcohol 80 mL/100 mL
INACTIVE INGREDIENTS: Glycerin; Hydrogen Peroxide; Water

Hand Sanitizer Gel

Drug Facts

Active Ingredient(s)

Alcohol 80% v/v

Purpose

Antiseptic

Use(s)

Hand sanitizer to help reduce bacteria that potentially can cause disease. For use when soap and water are not available.

Warnings

For external use only. Flammable. Keep away from heat or flame.

Do not use

- In children less than 2 months of age
- On open skin wounds

When using this product keep out of eyes, ears, and mouth. In case of contact with eyes, rinse thoroughly with water.

Stop use and ask a doctor if irritation or rash occurs. These may be signs of a serious condition.

Keep out of reach of children. If swallowed, get medical help or contact a Poison Control center right away.

Directions

- Place enough product on hands to cover all surfaces. Rub hands together until dry.
- Supervise children under 6 years of age when using this product to avoid swallowing.

Other Information

- Store between 15-30C (59-86F)
- Avoid freezing and excessive heat above 40C (104F)

Inactive Ingredients

glycerin, hydrogen peroxide, purified water USP

Questions?

www.ninemilehealth.com

Manufactured by Economy Polymers and Chemicals
435 E Anderson Road, Houston, TX 77047

Distributed by Nine Mile Health, LLC
5500 Greenwood Plaza Blvd., Suite 130, Greenwood Village, CO 80111

PRINCIPAL DISPLAY PANEL - 3785 mL Bottle Label

NINE MILE
HEALTH

GEL

ALCOHOL ANTISEPTIC 80%
TOPICAL SOLUTION

1
GALLON
(3785 mL)
| NON-STERILE SOLUTION